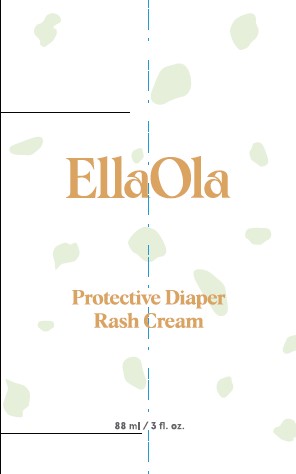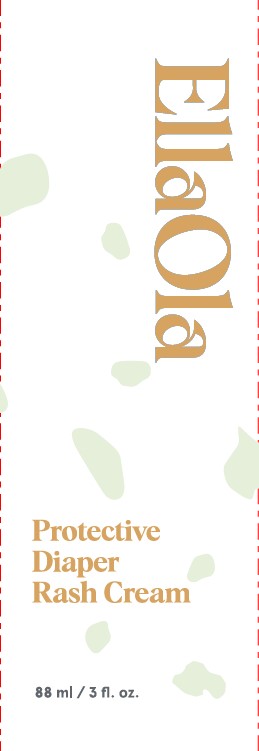 DRUG LABEL: Diaper Rash Cream
NDC: 82057-579 | Form: LOTION
Manufacturer: EllaOla Brands Inc.
Category: otc | Type: HUMAN OTC DRUG LABEL
Date: 20210629

ACTIVE INGREDIENTS: ZINC OXIDE 12 g/88 mL
INACTIVE INGREDIENTS: SUNFLOWER OIL; CASTOR OIL; CARNAUBA WAX

Active Ingredient

Zinc Oxide 14%

Warnings

Stop use and ask a doctor if condition worsens, symptoms last more than 7 days or clear up and occur again within a few days.

Warnings

Keep out of reach of children. If swallowed, get medical help or contact a Poison Control Center right away.

Purpose

Skin Protectant

Warnings

Keep out of reach of children. If swallowed, get medical help or contact a Poison Control Center right away.

Inactive Ingredients

Beeswax, Butyrospermum Parkii (Shea) Butter, Caprylic/Capric Triglyceride, Cocos Nucifera (Coconut) Oil, Copernicia Cerifera (Carnauba) Wax, Helianthus Annuus (Sunflower) Seed Oil, Laminaria Ochroleuca Extract, Polyglyceryl-2 Dipolyhydroxystearate, Ricinus Communis (Castor) Seed Oil

Uses

Helps treat and prevent diaper rash

Protects chafed skin due to diaper rash

Helps seal out wellness

Warnings

For external use only.

When using this product, do not get into eyes.

Stop use and ask a doctor if condition worsens, symptoms last more than 7 days or clear up and occur again within a few days

Keep out of reach of children. If swallowed, get medical help or contact a Poison Control Center right away.

Directions

Apply cream liberally as often as necessary with each diaper change, especially at bedtime or anytime when exposed to wet diapers may be prolonged.

Other information

Store at room tempreature and protect this product from direct sunlight.

Directions

Apply cream liberally as often as necessary with each diaper change, especially at bedtime or anytime when exposure to wet diapers maybe be prolonged.

PACKAGE LABEL

EllaOla Diaper Cream Tube 88mL NDC: 82057-579-01

EllaOla Diaper Cream Carton NDC: 82057-579-02